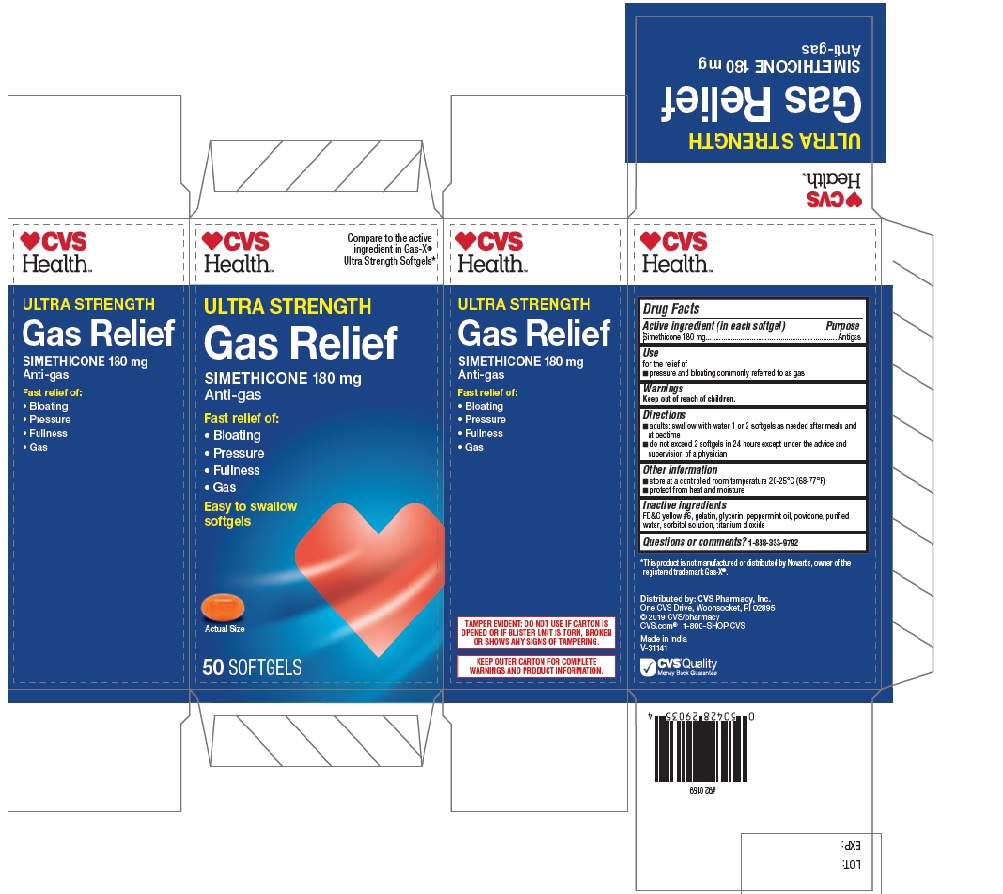 DRUG LABEL: CVS Health Ultra Strength Gas Relief
NDC: 69842-677 | Form: CAPSULE, LIQUID FILLED
Manufacturer: CVS Pharmacy
Category: otc | Type: HUMAN OTC DRUG LABEL
Date: 20241217

ACTIVE INGREDIENTS: DIMETHICONE 180 mg/1 1
INACTIVE INGREDIENTS: FD&C YELLOW NO. 6; GELATIN; GLYCERIN; PEPPERMINT OIL; POVIDONE K30; WATER; SORBITOL; TITANIUM DIOXIDE

CVS Health Ultra Strength Gas Relief

Drug Facts

Active ingredient (in each softgel)

Simethicone 180 mg

Purpose

Antigas

Uses

for the relief of
■ pressure and bloating commonly referred to as gas

Warnings

Keep out of reach of children.

Keep out of reach of children.

Directions

■adults: swallow with water 1 or 2 softgels as needed after meals and
at bedtime
■ do not exceed 2 softgels in 24 hours except under the advice and
supervision of a physician

Other information

■ store at a controlled room temperature 20-25°C (68-77°F)
■ protect from heat and moisture

Inactive ingredients

FD&C yellow #6, gelatin, glycerin, peppermint oil, povidone, purified
water, sorbitol solution, titanium dioxide

Questions or comments? 1-888-333-9792

PACKAGE LABEL

CVS Health Ultra Strength Gas Relief

Compare to the active
ingredient in Gas-X®
Ultra Strength Softgels*
Simethicone 180mg

Anti-gas

Fast Relief of:

Bloating

Pressure

Fullness

Gas

Easy to swallow softgels

50 Softgels

TAMPER EVIDENT: DO NOT USE IF CARTON IS
OPENED OR IF BLISTER UNIT IS TORN, BROKEN
OR SHOWS ANY SIGNS OF TAMPERING

KEEP OUTER CARTON FOR COMPLETE
WARNINGS AND PRODUCT INFORMATION.

*This product is not manufactured or distributed by Novartis, owner of the
registered trademark Gas-X®.

Distributed by: CVS Pharmacy, Inc.
One CVS Drive, Woonsocket, RI 02895
© 2019 CVS/pharmacy
CVS.com® 1-800-SHOP CVS
Made in India
V-31141